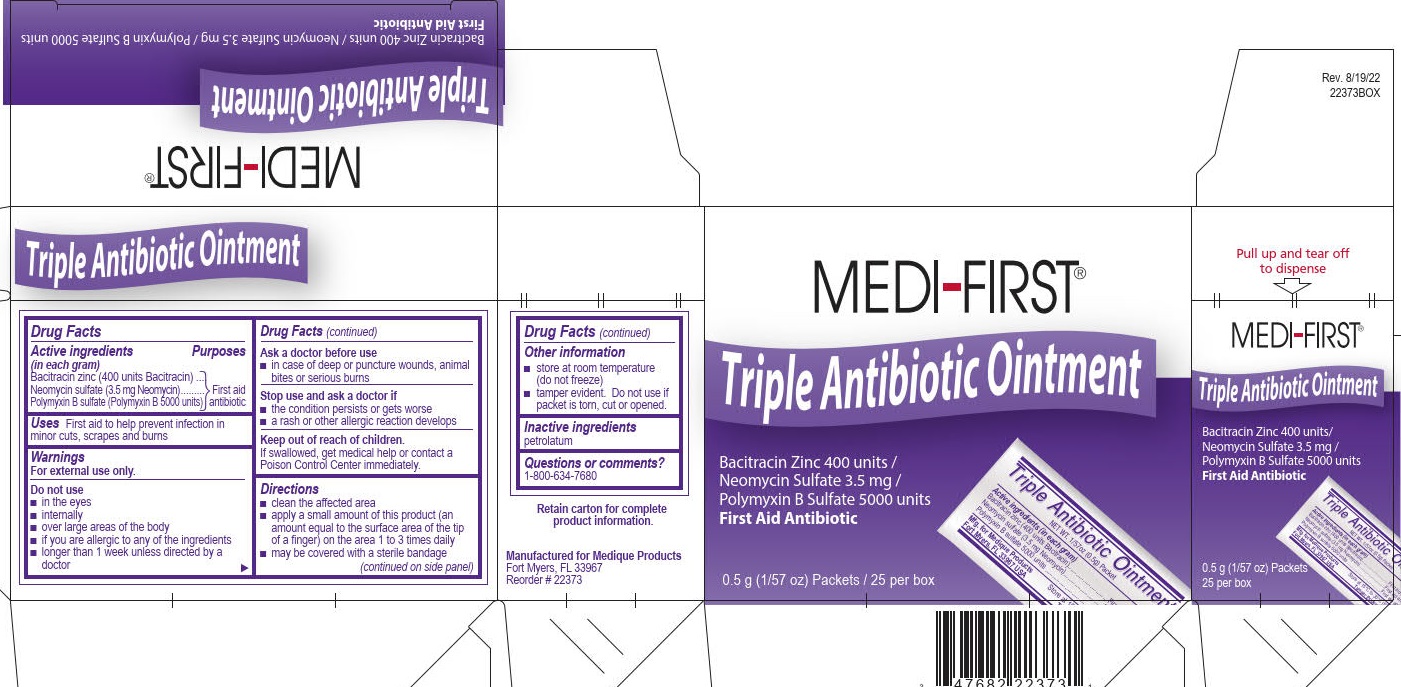 DRUG LABEL: Triple Antibiotic
NDC: 47682-223 | Form: OINTMENT
Manufacturer: Unifirst First Aid Corporation
Category: otc | Type: HUMAN OTC DRUG LABEL
Date: 20250908

ACTIVE INGREDIENTS: NEOMYCIN SULFATE 3.5 mg/1 g; POLYMYXIN B SULFATE 5000 [USP'U]/1 g; BACITRACIN ZINC 400 [USP'U]/1 g
INACTIVE INGREDIENTS: PETROLATUM

Medi-First Triple Antibiotic Ointment

Drug Facts

Active ingredients (each gram)

Bacitracin zinc (400 units Bacitracin)

Neomycin sulfate 5 mg (3.5 mg Neomycin)

Polymyxin-B sulfate (Polymyxin B 5000 units)

Purposes

First Aid Antibiotics

Uses

First aid to help prevent infection in minor cuts, scrapes and burns

Warnings

For external use only

Do not use

- in the eyes
- internally
- over large areas of the body
- if you are allergic to any of the ingredients
- longer than 1 week unless directed by a doctor

Ask a doctor before use

- in case of deep or puncture wounds, animal bites, or serious burns

Stop use and ask a doctor if

- the condition persists or gets worse
- a rash or other allergic reaction develops

Keep out of reach of children.

If swallowed, get medical help or contact a Poison Control Center immediately.

Directions

- clean the affected area
- apply a small amount of this product (an amount equal to the surface area of the tip of a finger) on the area 1 to 3 times daily
- may be covered with a sterile bandage

Other information

- store at room temperature (do not freeze)
- tamper evident. Do not use if packet is torn, cut or opened.

Inactive ingredients

petrolatum

Questions or comments? 1-800-634-7680

Medi-First Triple Antibiotic Ointment Label

Medi-First®

Triple Antibiotic Ointment

Bacitracin Zinc / Neomycin Sulfate / Polymycin B Sulfate

First Aid Antibiotic

First aid to help prevent infection in minor cuts, scrapes and burns

0.5g (1/57oz) Packets / 25 per box